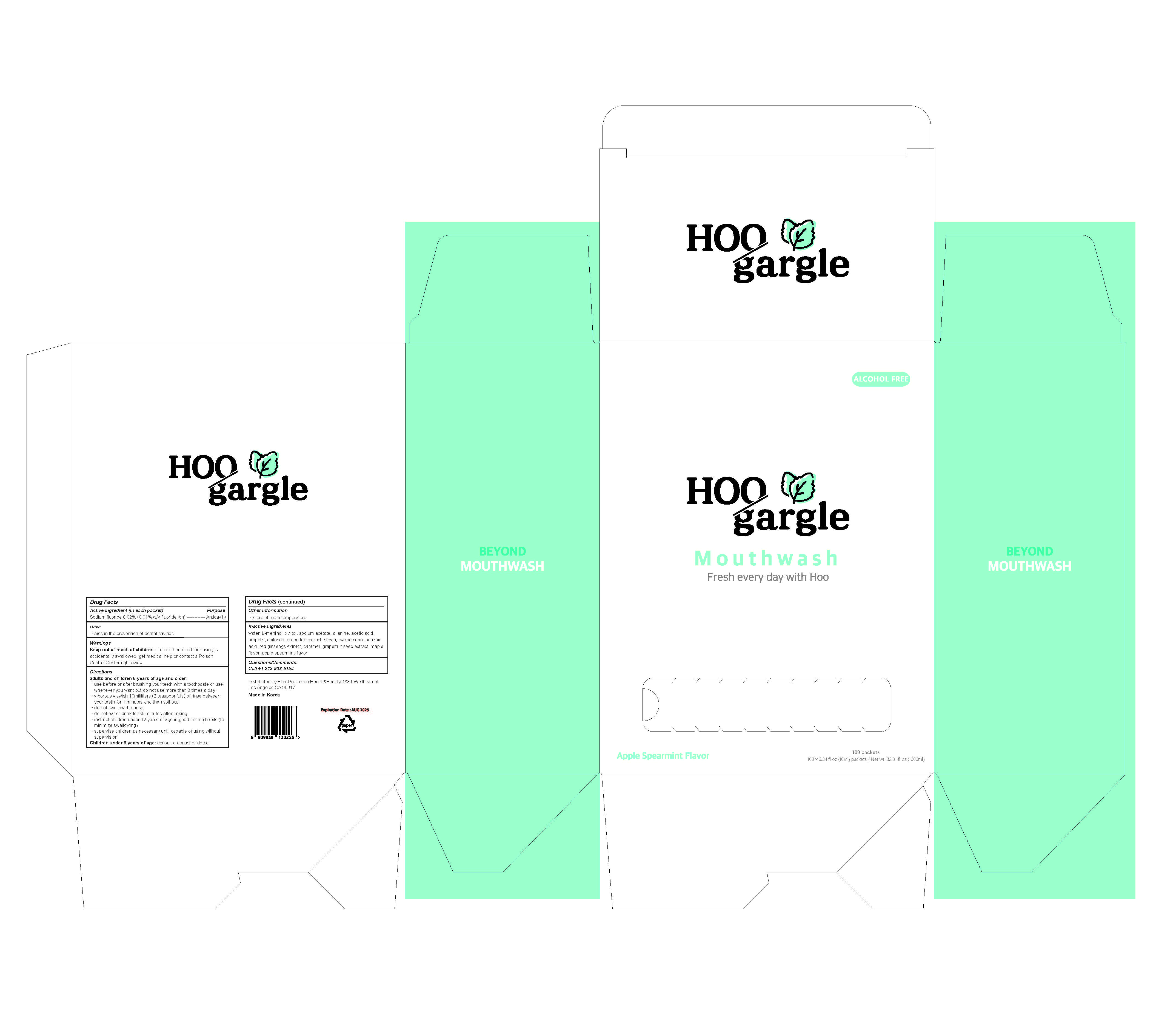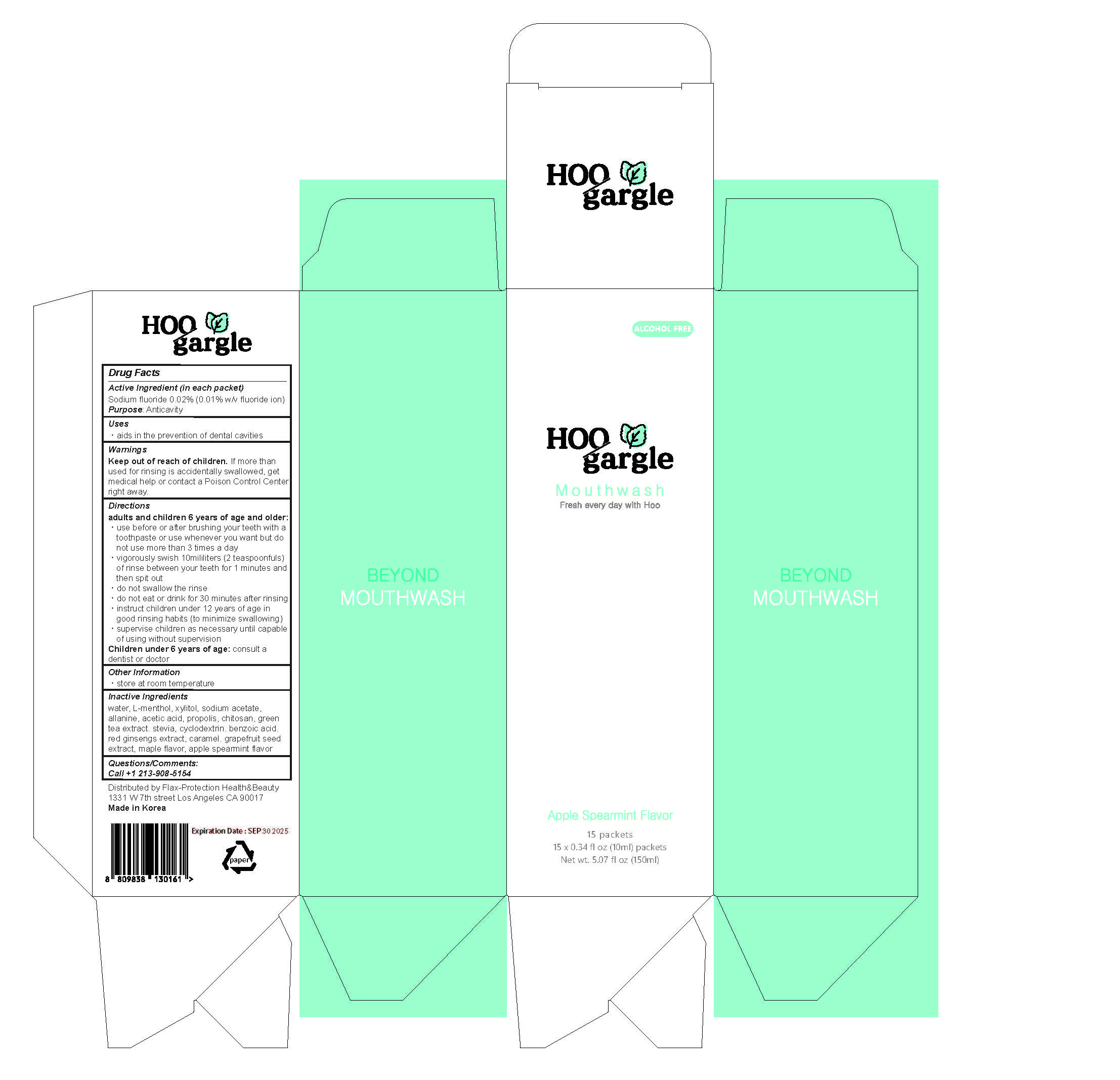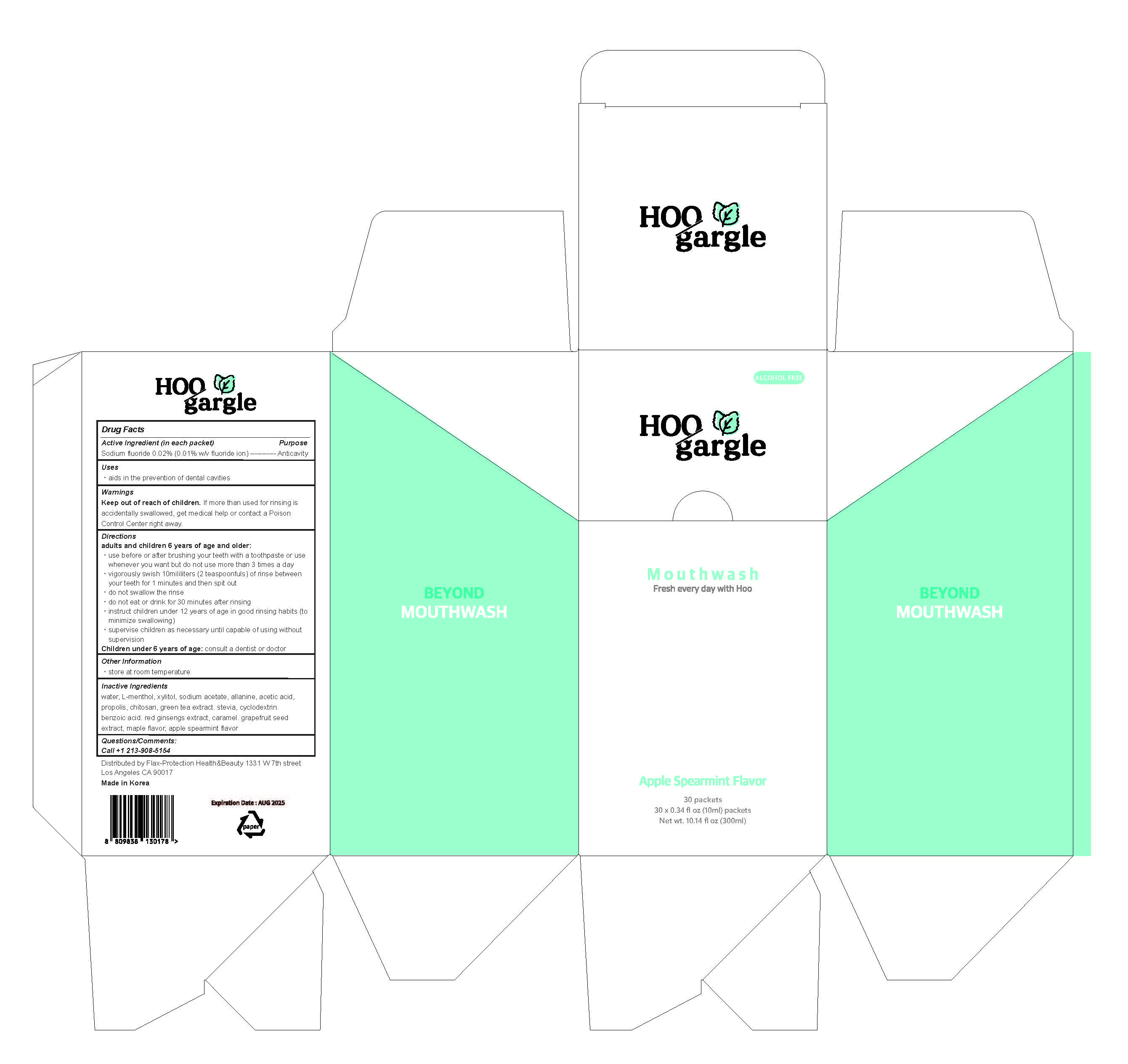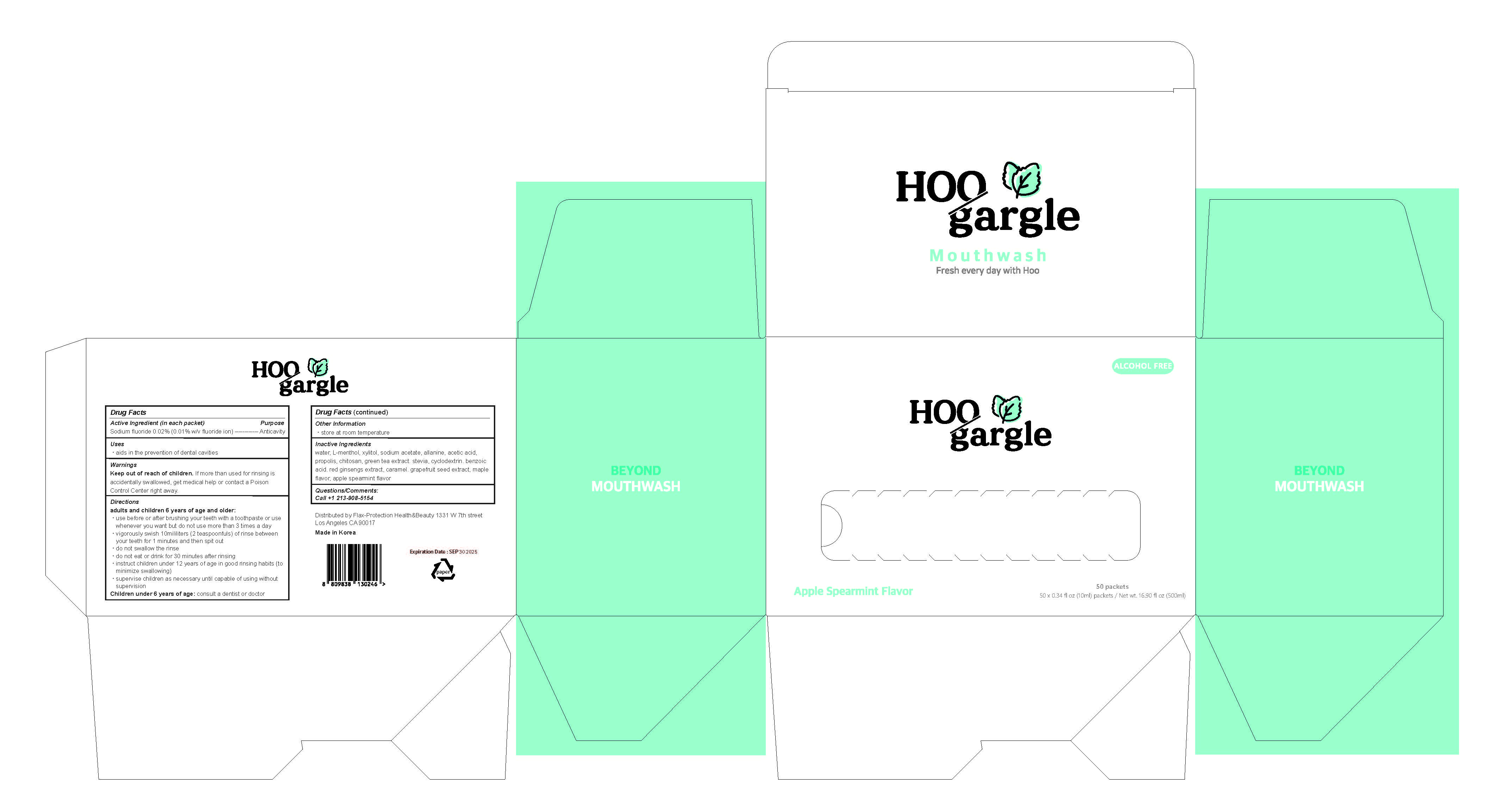 DRUG LABEL: Hoo Gargle Apple Spearmint Flavor
NDC: 83367-100 | Form: LIQUID
Manufacturer: Nuriearth Global Co., Ltd.
Category: otc | Type: HUMAN OTC DRUG LABEL
Date: 20230413

ACTIVE INGREDIENTS: SODIUM FLUORIDE 0.2 mg/1 mL
INACTIVE INGREDIENTS: XYLITOL 10 mg/1 mL; ALANINE 0.5 mg/1 mL; (2-AMINO-5,6-DICHLOROQUINAZOLIN-3(4H )-YL)ACETIC ACID 0.5 mg/1 mL; MENTHOL 0.6 mg/1 mL; SODIUM ACETATE 0.5 mg/1 mL

Hoo Gargle Apple Spearmint Flavor Active Ingredient

Sodium Flouride 0.02%

Hoo Gargle Apple Spearmint Flavor Ask Doctor

Children under 6 years of age: consult a dentist or doctor

Hoo Gargle Apple Spearmint Flavor Warning

Warnings

Keep out of reach of children. If more than used for rinsing is accidentally swallowed, get medical help or contact a Poison Control Center right away.

Hoo Gargle Apple Spearmint Flavor Keep Out of Reach of Children

Keep out of reach of children. If more than used for rinsing is accidentally swallowed, get medical help or contact a Poison Control Center right away.

Hoo Gargle Apple Spearmint Flavor Questions

Questions/Comments:

Call +1-203-908-5154

Hoo Gargle Apple Spearmint Flavor Directions

Directions

adults and children 6 years of age and older:

use before or after brushing your teeth with a toothpaste or use whenever you want but do not use more than 3 times a day
vigorously swish 10mililiters (2 teaspoonfuls) of rinse between your teeth for 1 minutes and then spit out
do not swallow the rinse
do not eat or drink for 30 minutes after rinsing
instruct children under 12 years of age in good rinsing habits (to minimize swallowing)
supervise children as necessary until capable of using without supervision

Hoo Gargle Apple Spearmint Flavor Inactive Ingredient

water, L-menthol, xylitol, sodium acetate, alanine, acetic acid, propolis, chitosan, green tea extract. stevia, cyclodextrin. benzoic acid. red ginsengs extract, caramel. grapefruit seed extract, maple flavor, apple spearmint flavor

Hoo Gargle Apple Spearmint Flavor Indications

aids in the prevention of dental cavities

Hoo Gargle Apple Spearmint Flavor Purpose

anticavity